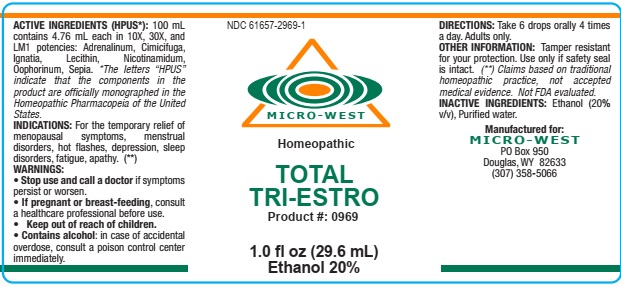 DRUG LABEL: Total Tri-Estro
NDC: 61657-0969 | Form: LIQUID
Manufacturer: White Manufacturing Inc. DBA Micro-West
Category: homeopathic | Type: HUMAN OTC DRUG LABEL
Date: 20190814

ACTIVE INGREDIENTS: EPINEPHRINE 10 [hp_X]/30 mL; BLACK COHOSH 10 [hp_X]/30 mL; STRYCHNOS IGNATII SEED  10 [hp_X]/30 mL; EGG PHOSPHOLIPIDS 10 [hp_X]/30 mL; NIACINAMIDE 10 [hp_X]/30 mL; SEPIA OFFICINALIS JUICE 10 [hp_X]/30 mL; ESTRADIOL 10 [hp_X]/30 mL; SUS SCROFA OVARY 10 [hp_X]/30 mL; ESTRIOL 10 [hp_X]/30 mL; ESTRONE 10 [hp_X]/30 mL
INACTIVE INGREDIENTS: POTASSIUM SORBATE; CITRIC ACID MONOHYDRATE

DRUG FACTS

ACTIVE INGREDIENTS

ALL INGREDIENTS ARE IN CONCENTRATES OF 10X, 30X, LM1:

ADRENALINUM
CIMICIFUGA
IGNATIA
LECITHIN

NICOTINAMIDUM

OOPHORINUM
SEPIA

PURPOSE

menopausal symptoms, menstrual disorders, hot flashes, depression, sleep disorders, fatigue, apathy

KEEP OUT OF REACH OF CHILDREN

INDICATIONS

INDICATIONS: fOR THE TEMPORARY RELIEF of menopausal symptoms, menstrual disorders, hot flashes, depression, sleep disorders, fatigue, apathy

WARNINGS

WARNING: STOP USE AND CALL A DOCTOR if symptoms persist or worsen. CONTAINS ALCOHOL: in case of accidental overdose, consult a poison control center immediately

OTHER INFORMATION: Tamper resistant for your protection. Use only if safety seal is intact.

DIRECTIONS

DIRECTIONS: Take 2 pump sprays 3 times daily. hold under tongue for 30 seconds before swallowing. More frequent dosages may be used according to symptomatic needs. For adults only

INACTIVE INGREDIENTS

Potassium sorbate

Citric acid

Purified water

MANUFACTURED FOR

MICRO-WEST

P.O. Box 950

DOUGLAS, WY 82633

1-307-358-5066

LABEL

NDC 61657-2969-1

MICRO-WEST

Homeopathic

TOTAL

TRI-ESTRO

Product #: 0969

1.0 fl oz (29.6 mL)

Ethanol 20%